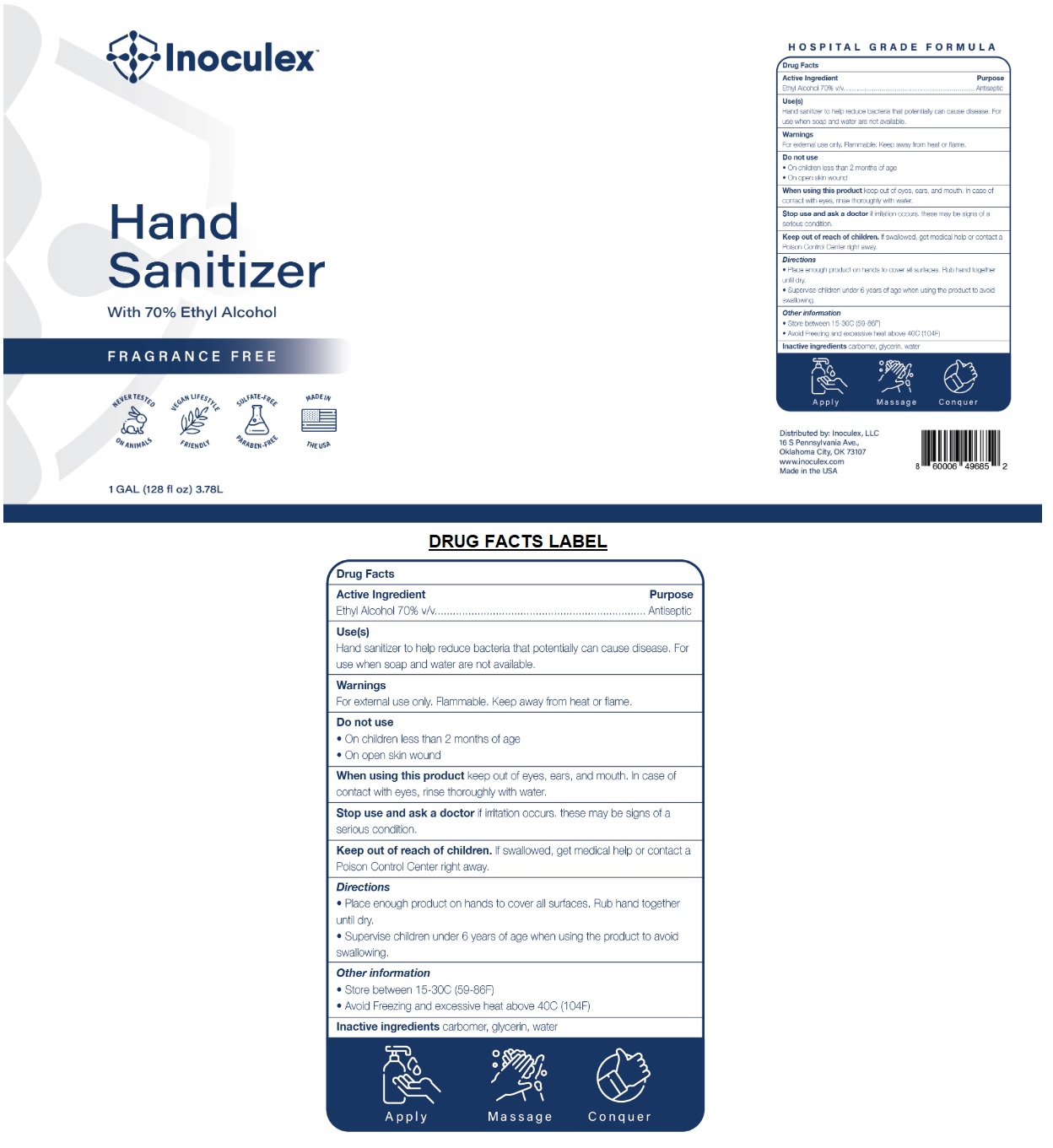 DRUG LABEL: Inoculex Hand Sanitizer
NDC: 77017-014 | Form: GEL
Manufacturer: Private Label Supplements, Llc
Category: otc | Type: HUMAN OTC DRUG LABEL
Date: 20210304

ACTIVE INGREDIENTS: ALCOHOL 70 L/100 L
INACTIVE INGREDIENTS: CARBOMER HOMOPOLYMER, UNSPECIFIED TYPE; GLYCERIN; WATER

Inoculex™ Hand Sanitizer

Active Ingredient

Ethyl Alcohol 70% v/v

Purpose

Antiseptic

Use(s)

Hand sanitizer to help reduce bacteria that potentially can cause disease. For use when soap and water are not available.

Warnings

For external use only. Flammable. Keep away from heat or flame.

Do not use

• On children less than 2 months of age

• On open skin wound

When using this product keep out of eyes, ears, and mouth. In case of contact with eyes, rinse thoroughly with water.

Stop use and ask a doctor if irritation occurs. these may be signs of a serious condition.

Keep out of reach of children. If swallowed, get medical help or contact a Poison Control Center right away.

Directions

• Place enough product on hands to cover all surfaces. Rub hand together until dry.

• Supervise children under 6 years of age when using the product to avoid swallowing.

Other information

• Store between 15-30C (59-86F)

• Avoid Freezing and excessive heat above 40C (104F)

Inactive ingredients

carbomer, glycerin, water

With 70% Ethyl Alcohol

FRAGRANCE FREE

NEVER TESTED ON ANIMALS

VEGAN LIFESTYLE FRIENDLY

SULFATE-FREE

PARABEN-FREE

HOSPITAL GRADE FORMULA

Apply Massage Conquer

Distributed by: Inoculex, LLC

16 S Pennsylvania Ave.,

Oklahoma City, OK 73107

www.inoculex.com

Made in the USA